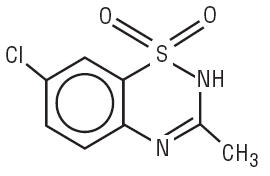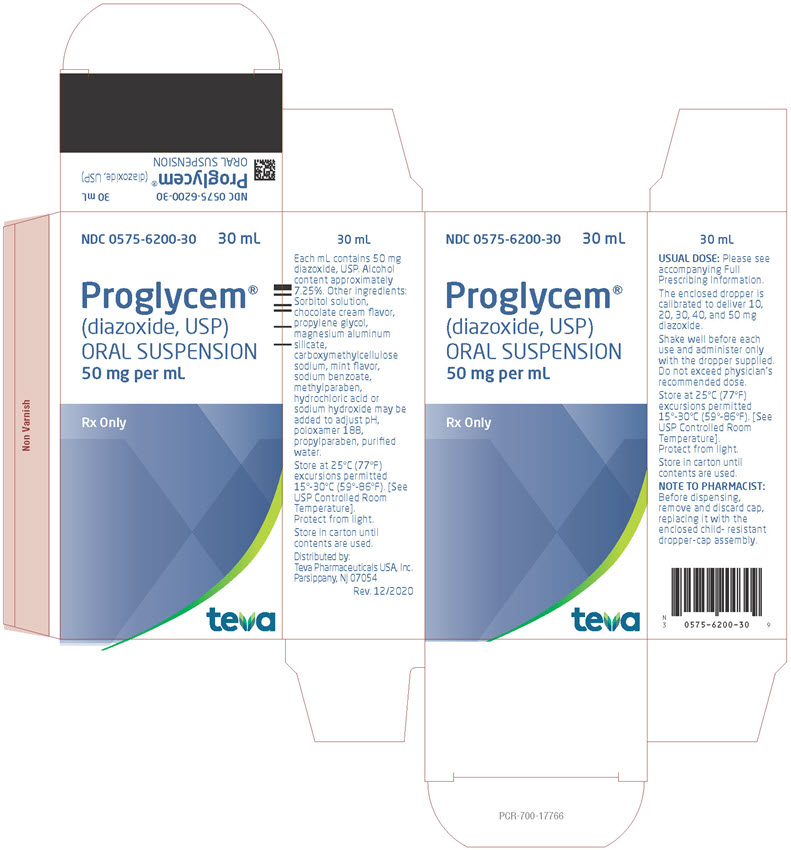 DRUG LABEL: Proglycem
NDC: 0575-6200 | Form: SUSPENSION
Manufacturer: Teva Pharmaceuticals USA, Inc.
Category: prescription | Type: HUMAN PRESCRIPTION DRUG LABEL
Date: 20240719

ACTIVE INGREDIENTS: DIAZOXIDE 50 mg/1 mL
INACTIVE INGREDIENTS: SORBITOL; PROPYLENE GLYCOL; MAGNESIUM ALUMINUM SILICATE; CARBOXYMETHYLCELLULOSE SODIUM; SODIUM BENZOATE; METHYLPARABEN; POLOXAMER 188; PROPYLPARABEN; ALCOHOL; HYDROCHLORIC ACID; SODIUM HYDROXIDE; WATER

PROGLYCEM®
(diazoxide)
oral suspension

DESCRIPTION

PROGLYCEM® (diazoxide) oral suspension is a nondiuretic benzothiadiazine derivative taken orally for the management of symptomatic hypoglycemia. PROGLYCEM oral suspension contains 50 mg of diazoxide in each milliliter and has a chocolate-mint flavor; alcohol content is approximately 7.25%. Other ingredients include sorbitol solution, chocolate cream flavor, propylene glycol, magnesium aluminum silicate, carboxymethylcellulose sodium, mint flavor, sodium benzoate, methylparaben, poloxamer 188, propylparaben, and purified water. Hydrochloric acid or sodium hydroxide may be added to adjust pH.

Diazoxide has the following structural formula:

Diazoxide is 7-chloro-3-methyl-2H-1,2,4-benzothiadiazine 1,1-dioxide with the empirical formula C8H7ClN2O2S and the molecular weight 230.7. It is a white powder practically insoluble to sparingly soluble in water.

CLINICAL PHARMACOLOGY

PROGLYCEM produces a dose-related increase in blood glucose, due primarily to an inhibition of insulin release from the pancreas, and also to an extrapancreatic effect.

The hyperglycemic effect of PROGLYCEM begins within an hour and generally lasts no more than 8 hours in the presence of normal renal function.

PROGLYCEM decreases the excretion of sodium and water, resulting in fluid retention which may be clinically significant.

The hypotensive effect of PROGLYCEM is usually not marked (see ADVERSE REACTIONS).

Other pharmacologic actions of PROGLYCEM include increased pulse rate; increased serum uric acid levels due to decreased excretion; increased serum levels of free fatty acids’ decreased chloride excretion; decreased para-aminohippuric acid; (PAH) clearance with no appreciable effect on glomerular filtration rate.

The concomitant administration of a benzothiazide diuretic may intensify the hyperglycemic and hyperuricemic effects of PROGLYCEM. In the presence of hypokalemia, hyperglycemic effects are also potentiated.

PROGLYCEM-induced hyperglycemia is reversed by the administration of insulin or tolbutamide. The inhibition of insulin release by PROGLYCEM is antagonized by alpha-adrenergic blocking agents.

PROGLYCEM is extensively bound (more than 90%) to serum proteins and is excreted in the kidneys. The plasma half-life following intravenous administration is 28 ± 8.3 hours. Limited data on oral administration revealed a half-life of 24 and 36 hours in two adults. In four children aged 4 months to 6 years, the plasma half-life varied from 9.5 to 24 hours on long-term oral administration. The half-life may be prolonged following overdosage, and in patients with impaired renal function.

INDICATIONS AND USAGE

PROGLYCEM is indicated for the management of hypoglycemia due to hyperinsulinism associated with the following conditions:

- Adults: Inoperable islet cell adenoma or carcinoma, or extrapancreatic malignancy.
- Infants and children: Leucine sensitivity, islet cell hyperplasia, nesidioblastosis, extrapancreatic malignancy, islet cell adenoma, or adenomatosis. PROGLYCEM may be used preoperatively as a temporary measure, and postoperatively, if hypoglycemia persists.

PROGLYCEM should be used only after a diagnosis of hypoglycemia due to one of the above conditions has been definitely established. When other specific medical therapy or surgical management either has been unsuccessful or is not feasible, treatment with PROGLYCEM should be considered.

CONTRAINDICATIONS

PROGLYCEM is contraindicated in patients with:

- Functional hypoglycemia
- Hypersensitivity to diazoxide, any of the excipients in PROGLYCEM, or other thiazides

WARNINGS

The antidiuretic property of diazoxide may lead to significant fluid retention. In patients with compromised cardiac reserve, fluid retention may precipitate congestive heart failure. If fluid retention develops, manage according to standards of care.

Co-administration of PROGLYCEM with thiazides may potentiate the hyperglycemic and hyperuricemic actions of diazoxide (see DRUG INTERACTIONS and ANIMAL PHARMACOLOGY AND/OR TOXICOLOGY).

Ketoacidosis and nonketotic hyperosmolar coma have been reported in patients treated with PROGLYCEM, usually during intercurrent illness. Prompt recognition and treatment are essential (see OVERDOSAGE), and prolonged surveillance following the acute episode is necessary because of the long drug half-life of approximately 30 hours. Advise patients to monitor urine glucose and ketones and to promptly report abnormal findings and symptoms of ketoacidosis to their healthcare provider. Transient cataracts occurred in association with hyperosmolar coma in an infant, and subsided on correction of the hyper-osmolarity. Cataracts have been observed in several animals receiving daily dosages of intravenous or oral diazoxide.

The development of abnormal facial features in four children treated chronically (>4 years) with PROGLYCEM for hypoglycemia hyperinsulinism in the same clinic has been reported.

Pulmonary Hypertension in Neonates and Infants

There have been postmarketing reports of pulmonary hypertension occurring in infants and neonates treated with diazoxide. The cases were reversible upon discontinuation of diazoxide. Monitor patients, especially those with risk factors for pulmonary hypertension, for respiratory distress and discontinue PROGLYCEM if pulmonary hypertension is suspected.

PRECAUTIONS

General

Treatment with PROGLYCEM should be initiated under close clinical supervision, with careful monitoring of blood glucose and clinical response until the patient’s condition has stabilized. This usually requires several days. If not effective in 2 to 3 weeks, discontinue PROGLYCEM.

Prolonged treatment requires regular monitoring of urine glucose and ketones, especially under stress conditions. Advise patients to promptly report any abnormalities to their healthcare provider. Periodically monitor blood glucose to determine the need for dosage adjustment.

Consider the effects of PROGLYCEM on the hematopoietic system and the level of serum uric acid; the latter should be considered particularly in patients with hyperuricemia or a history of gout.

Since the plasma half-life of diazoxide is prolonged in patients with impaired renal function, a reduced dosage should be considered. Serum electrolyte levels should also be evaluated for such patients.

The antihypertensive effect of other drugs may be enhanced by PROGLYCEM, and this should be kept in mind when administering it concomitantly with antihypertensive agents.

Because of the protein binding, administration of PROGLYCEM with coumarin anticoagulants or its derivatives may require reduction in the dosage of the anticoagulant, although there has been no reported evidence of excessive anticoagulant effect. In addition, PROGLYCEM may displace bilirubin from albumin; consider this when treating newborns with increased bilirubinemia.

Pulmonary hypertension has been reported in neonates and young infants treated with diazoxide (see WARNINGS).

Information for Patients

Advise patients of the need for periodic laboratory testing during treatment with PROGLYCEM. In addition, advise patients to:

- take PROGLYCEM on a regular schedule as prescribed, not to skip doses, not to take extra doses
- consult their healthcare provider before starting any new medications
- not allow anyone else to take this medication
- follow dietary instructions
- report any adverse reactions (i.e., increased urinary frequency, increased thirst, fruity breath odor) promptly to their healthcare provider
- report pregnancy or to discuss plans for pregnancy with their healthcare provider

Laboratory Tests

Consider monitoring the following laboratory tests during treatment with PROGLYCEM (not all-inclusive):

- blood glucose (recommended at periodic intervals in patients taking diazoxide orally for treatment of hypoglycemia, until stabilized)
- blood urea nitrogen (BUN) and creatinine clearance
- hematocrit, platelet count, total and differential leukocyte counts
- serum aspartate aminotransferase (AST)
- serum uric acid level
- urine testing for glucose and ketones

Drug Interactions

Since diazoxide is highly bound to serum proteins, it may displace other substances which are also bound to protein, such as bilirubin or coumarin and its derivatives, resulting in higher blood levels of these substances. Concomitant administration of PROGLYCEM and diphenylhydantoin may result in a loss of seizure control. Consider these potential interactions when administering PROGLYCEM.

The concomitant administration of thiazides or other diuretics may potentiate the hyperglycemic and hyperuricemic effects of PROGLYCEM.

Drug/Laboratory Test Interactions

The hyperglycemic and hyperuricemic effects of diazoxide preclude proper assessment of these metabolic states. Increased renin secretion, IgG concentrations and decreased cortisol secretions have also been noted. Diazoxide inhibits glucagon-stimulated insulin release and causes a false-negative insulin response to glucagon.

Carcinogenesis, Mutagenesis, Impairment of Fertility

No long-term animal dosing study has been done to evaluate the carcinogenic potential of diazoxide. No laboratory study of mutagenic potential or animal study of effects on fertility has been done.

Reproduction studies using the oral preparation in rats have revealed increased fetal resorptions and delayed parturition, as well as fetal skeletal anomalies; evidence of skeletal and cardiac teratogenic effects in rabbits has been noted with intravenous administration. Diazoxide has also been demonstrated to cross the placental barrier in animals and to cause degeneration of the fetal pancreatic beta cells (see ANIMAL PHARMACOLOGY AND/OR TOXICOLOGY). Since there are no adequate data on fetal effects of this drug when given to pregnant women, safety in pregnancy has not been established. When the use of PROGLYCEM is considered, the indications should be limited to those specified above for adults (see INDICATIONS AND USAGE), and the potential benefits to the mother must be weighed against possible harmful effects to the fetus.

Non-teratogenic Effects

Diazoxide crosses the placental barrier and appears in cord blood. When given to the mother prior to delivery of the infant, diazoxide may produce fetal or neonatal hyperbilirubinemia, thrombocytopenia, altered carbohydrate metabolism, and possibly other side effects that have occurred in adults.

Alopecia and hypertrichosis lanuginosa have occurred in infants whose mothers received oral diazoxide during the last 19 to 60 days of pregnancy.

Labor and Delivery

Since intravenous administration of PROGLYCEM during labor may cause cessation of uterine contractions, and administration of oxytocic agents may be required to reinstate labor, caution is advised in administering PROGLYCEM at that time.

Nursing Mothers

Information is not available concerning the passage of diazoxide in breast milk. Because many drugs are excreted in human milk and because of the potential for adverse reactions from diazoxide in nursing infants, a decision should be made whether to discontinue nursing or to discontinue PROGLYCEM, taking into account the importance of the use of PROGLYCEM in the mother.

Pediatric Use

See INDICATIONS AND USAGE.

ADVERSE REACTIONS

Frequent and Serious:

Sodium and fluid retention is most common in young infants and in adults and may precipitate congestive heart failure in patients with compromised cardiac reserve (see DRUG INTERACTIONS).

Infrequent but Serious:

Diabetic ketoacidosis and hyperosmolar nonketotic coma may develop very rapidly. Monitor patients for up to 7 days due to the long half-life of PROGLYCEM (see OVERDOSAGE).

Other frequent adverse reactions:

Hirsutism of the lanugo type, mainly on the forehead, back and limbs, occurs most commonly in children and women and may be cosmetically unacceptable. It subsides on discontinuation of PROGLYCEM.

Hyperglycemia or glycosuria may require reduction in dosage in order to avoid progression to ketoacidosis or hyperosmolar coma.

Gastrointestinal intolerance may include anorexia, nausea, vomiting, abdominal pain, ileus, diarrhea, transient loss of taste.

Tachycardia, palpitations, increased levels of serum uric acid are common.

Thrombocytopenia with or without purpura may require discontinuation of PROGLYCEM. Neutropenia is transient, is not associated with increased susceptibility to infection, and ordinarily does not require discontinuation of PROGLYCEM. Skin rash, headache, weakness, and malaise may also occur.

Other adverse reactions:

Cardiovascular: Hypotension occurs occasionally, which may be augmented by thiazide diuretics given concurrently. A few cases of transient hypertension, for which no explanation is apparent, have been noted. Chest pain has been reported rarely. Pulmonary hypertension has been reported in neonates and young infants (see WARNINGS).

There have been postmarketing reports of pericardial effusion in patients without structural heart disease; the majority of cases occurred in pediatric patients and infants.

Gastrointestinal: There have been postmarketing reports of necrotizing enterocolitis; the majority of cases occurred in infants with underlying co-morbid conditions.

Hematologic: eosinophilia; decreased hemoglobin / hematocrit; excessive bleeding, decreased IgG.

Hepato-renal: increased AST, alkaline phosphatase; azotemia, decreased creatinine clearance, reversible nephrotic syndrome, decreased urinary output, hematuria, albuminuria. Neurologic: anxiety, dizziness, insomnia, polyneuritis, paresthesia, pruritus, extrapyramidal signs.

Ophthalmologic: transient cataracts, subconjunctival hemorrhage, ring scotoma, blurred vision, diplopia, lacrimation.

Skeletal, integumentary; monilial dermatitis, herpes, advance in bone age; loss of scalp hair.

Systemic: fever, lymphadenopathy.

Other; gout acute pancreatitis/pancreatic necrosis, galactorrhea, enlargement of lump in breast.

OVERDOSAGE

An overdosage of PROGLYCEM causes marked hyperglycemia which may be associated with ketoacidosis. Because of the diazoxide’s long half-life (approximately 30 hours), the symptoms of overdosage require prolonged surveillance for periods up to 7 days until the blood glucose level stabilizes within the normal range. One investigator reported successful lowering of diazoxide blood levels by peritoneal dialysis in one patient and by hemodialysis in another.

DOSAGE AND ADMINISTRATION

Patients should be under close clinical observation when treatment with PROGLYCEM is initiated. Carefully monitor the clinical response and blood glucose until the patient’s condition has stabilized satisfactory; in most instances, this may be accomplished in several days. If administration of PROGLYCEM is not effective after 2 or 3 weeks, discontinue PROGLYCEM.

Individualize the dosage of PROGLYCEM based on the severity of the hypoglycemic condition and the blood glucose level and clinical response of the patient. Adjust the dosage until the desired clinical and laboratory effects are produced with the least amount of PROGLYCEM. Take special care to ensure the accuracy of the dosage in infants and young children.

Adults and children:

The recommended starting dosage is 3 mg/kg/day, administered orally, divided into 3 equal doses every 8 hours or 2 equal doses every 12 hours. The dosage may be titrated to a maximum of 8 mg/kg/day. Patients with refractory hypoglycemia may require higher dosages.

Infants and newborns:

The recommended starting dosage is 8 mg/kg/day, administered orally, divided into 3 equal doses every 8 hours or 2 equal doses every 12 hours. The dosage may be titrated to a maximum of 15 mg/kg/day.

ANIMAL PHARMACOLOGY AND/OR TOXICOLOGY

Oral diazoxide in the mouse, rat, rabbit, dog, pig, and monkey produces a rapid and transient rise in blood glucose levels. In dogs, increased blood glucose is accompanied by increased free fatty acids, lactate, and pyruvate in the serum. In mice, a marked decrease in liver glycogen and an increase in the blood urea nitrogen level occur.

In acute toxicity studies the LD50 for orally administered diazoxide is >5,000 mg/kg in the rat, >522 mg/kg in the neonatal rat, between 1,900 and 2,572 mg/kg in the mouse, and 219 mg/kg in the guinea pig. Although the oral LD50 was not determined in the dog, a dosage of up to 500 mg/kg was well tolerated.

In subacute oral toxicity studies, diazoxide at 400 mg/kg in the rat produced growth retardation, edema, increases in liver and kidney weights, and adrenal hypertrophy. Daily dosages up to 1,080 mg/kg for 3 months produced hyperglycemia, an increase in liver weight and an increase in mortality. In dogs given oral diazoxide at approximately 40 mg/kg/day for 1 month, no biologically significant gross or microscopic abnormalities were observed. Cataracts, attributed to markedly disturbed carbohydrate metabolism, have been observed in a few dogs given repeated daily dosages of oral or intravenous diazoxide. The lenticular changes resembled those which occur experimentally in animals with increased blood glucose levels. In chronic toxicity studies, rats given a daily dosage of 200 mg/kg diazoxide for 52 weeks had a decrease in weight gain and an increase in heart, liver, adrenal and thyroid weights. Mortality in drug-treated and control groups was not different. Dogs treated with diazoxide at dosages of 50, 100, and 200 mg/kg/day for 82 weeks had higher blood glucose levels than controls. Mild bone marrow stimulation and increased pancreas weights were evident in diazoxide-treated dogs; several developed inguinal hernias, one had a testicular seminoma, and another had a mass near the penis. Two females had inguinal mammary swellings. The etiology of these changes was not established. There was no difference in mortality between diazoxide-treated and control groups. In a second chronic oral toxicity study, dogs given milled diazoxide dosages of 50, 100, and 200 mg/kg/day had anorexia and severe weight loss, causing death in a few. Hematologic, biochemical, and histologic examination did not indicate any cause of death other than inanition. After 1 year of treatment, there is no evidence of herniation or tissue swelling in any of the dogs.

When diazoxide was administered at high dosages concomitantly with either chlorothiazide to rats or trichlormethiazide to dogs, increased toxicity was observed. In rats, the combination was nephrotoxic; epithelial hyperplasia was observed in the collecting tubules. In dogs, a diabetic syndrome was produced which resulted in ketosis and death. Neither of the drugs given alone produced these effects.

Although the data are inconclusive, reproduction and teratology studies in several species of animals indicate that diazoxide, when administered during the critical period of embryo formation, may interfere with normal fetal development, possibly through altered glucose metabolism. Parturition was occasionally prolonged in animals treated at term. Intravenous administration of diazoxide to pregnant sheep, goats, and swine produced in the fetus an appreciable increase in blood glucose level and degeneration of the beta cells of the Islets of Langerhans. The reversibility of these effects was not studied.

HOW SUPPLIED

PROGLYCEM (diazoxide) oral suspension, 50 mg/mL, a chocolate-mint flavored suspension; bottle of 30 ml (NDC 0575-6200-30), with dropper calibrated to deliver 10, 20, 30, 40 and 50 mg diazoxide.

Shake well before each use. Protect from light. Store in carton until contents are used. Store in light resistant container as defined in the USP. Store PROGLYCEM at 25°C (77°F) excursions permitted to 15°C to 30°C (59°F to 86°F). See USP Controlled Room Temperature.

Manufactured for:
Teva Pharmaceuticals
Parsippany, NJ 07054

©2024 Teva Pharmaceuticals USA, Inc.

Rev. 7/2024

PRGM-003

Package/Label Display Panel

NDC 0575-6200-30 30 mL

Proglycem (diazoxide, USP) ORAL SUSPENSION

50 mg per mL

Rx Only

TEVA